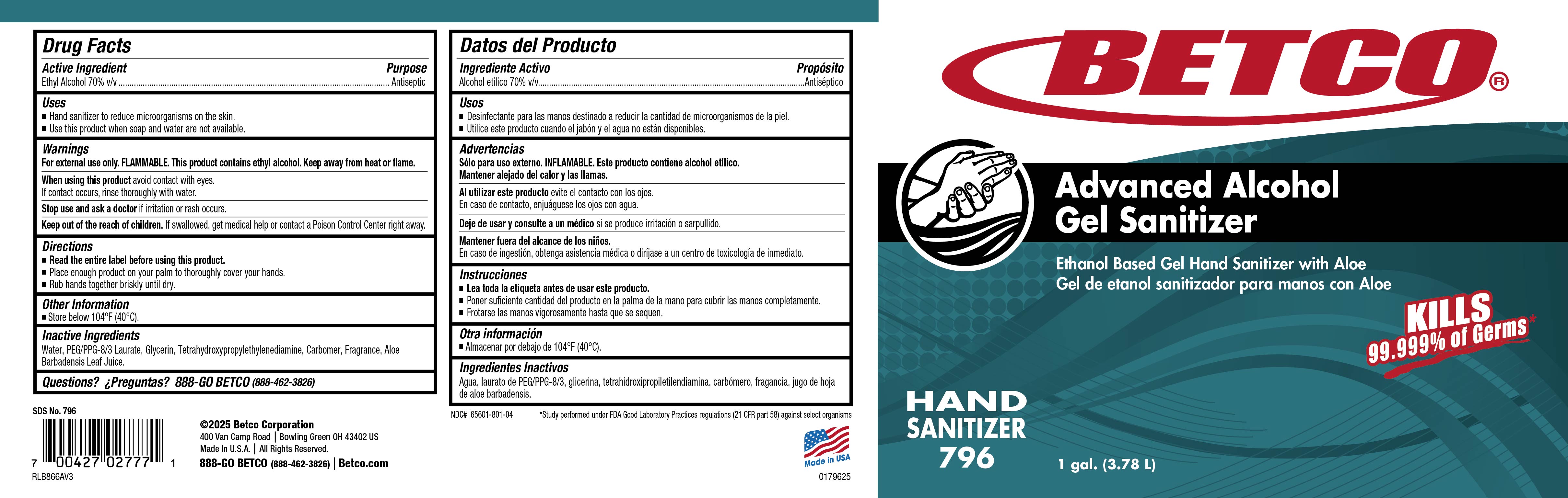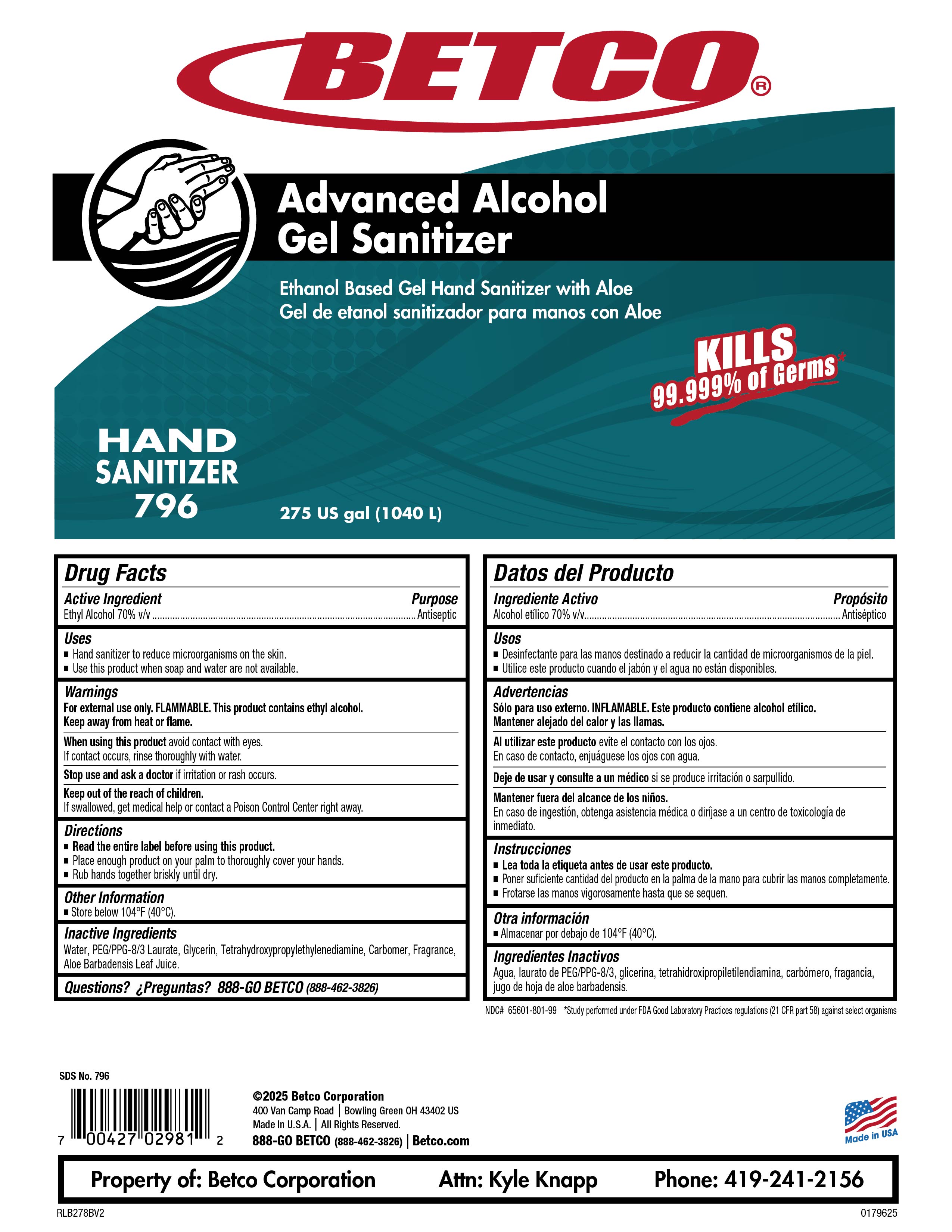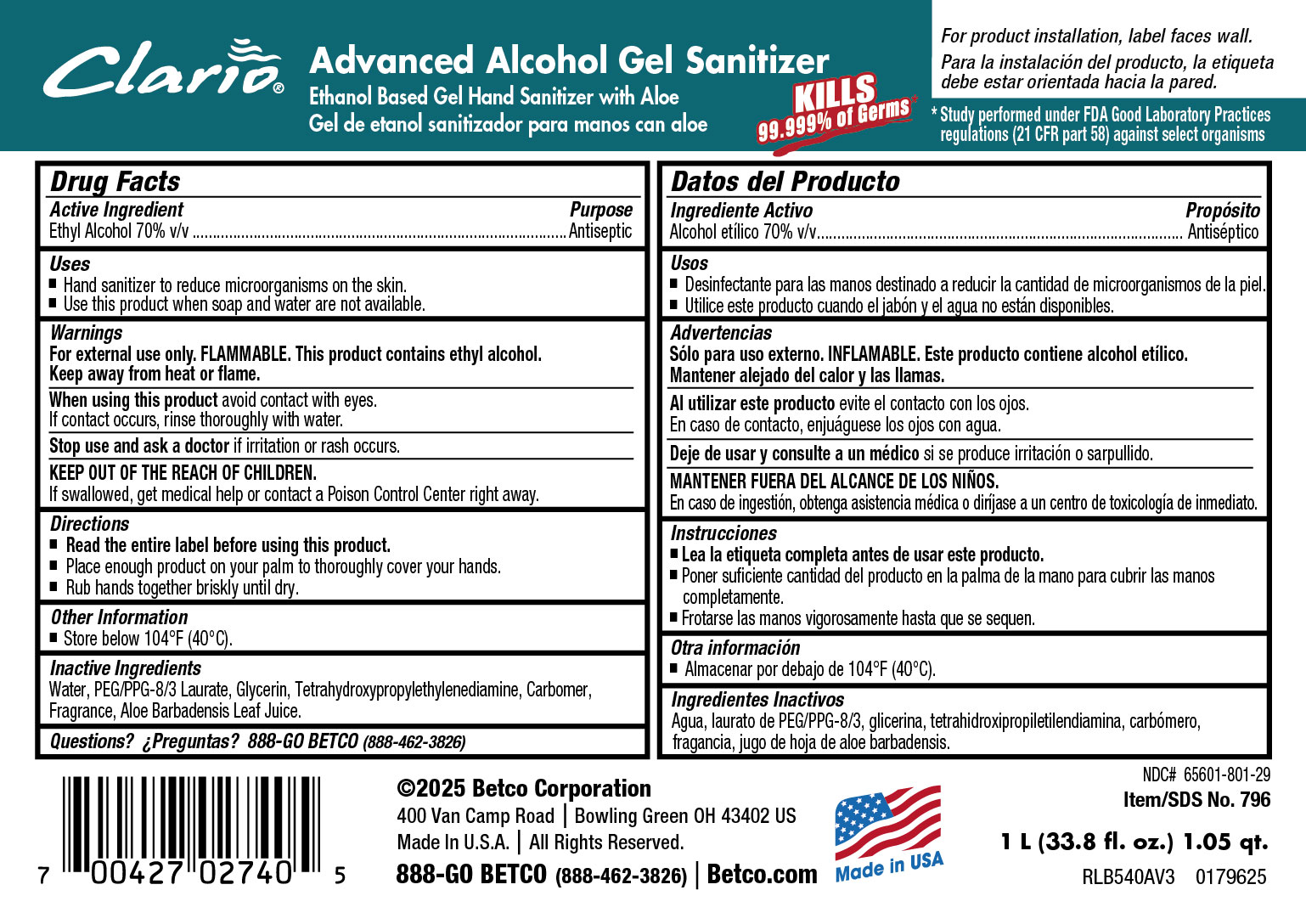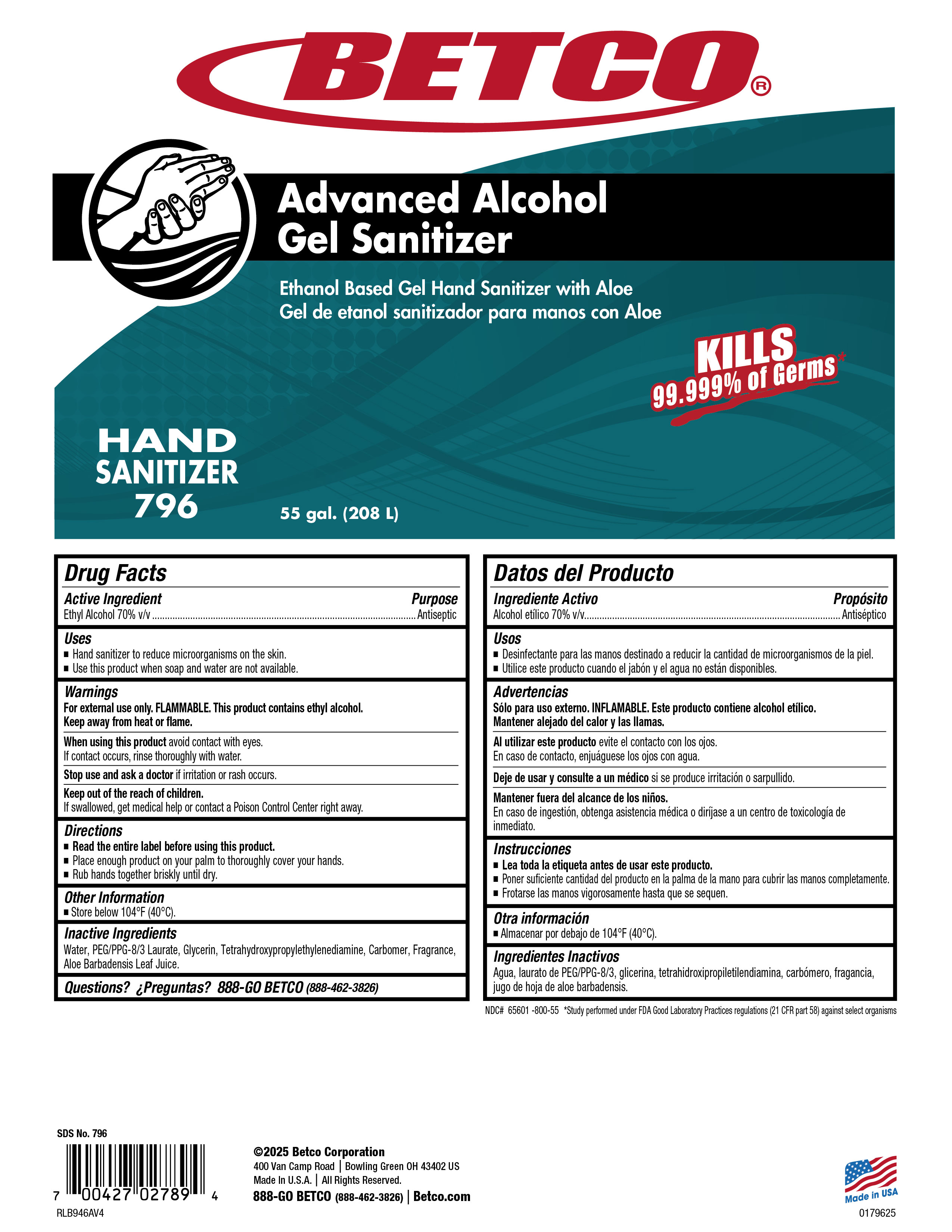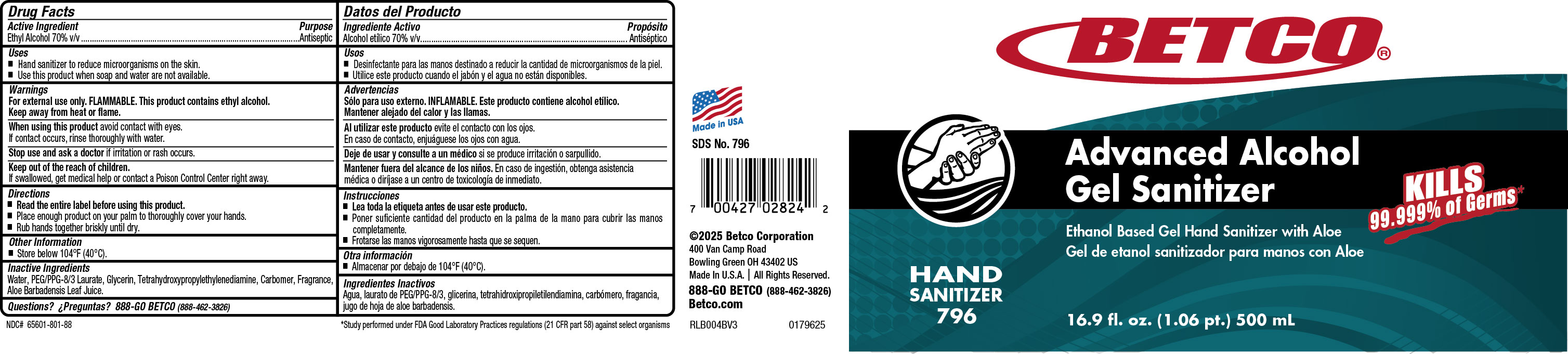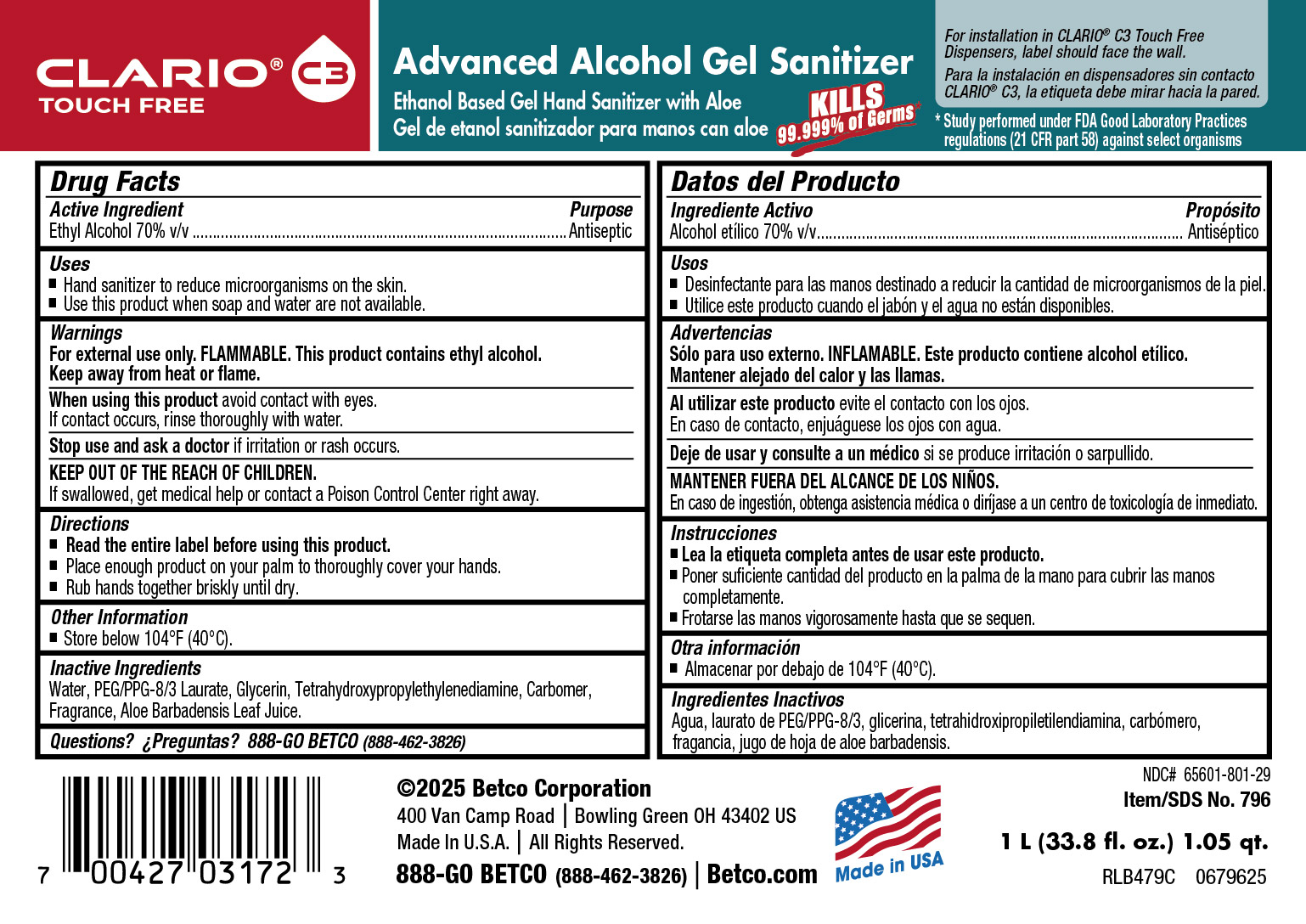 DRUG LABEL: Advanced Alcohol Gel Sanitizer
NDC: 65601-801 | Form: GEL
Manufacturer: Betco Corporation, Ltd
Category: otc | Type: HUMAN OTC DRUG LABEL
Date: 20260217

ACTIVE INGREDIENTS: ALCOHOL 0.7 mL/1 mL
INACTIVE INGREDIENTS: HEXYL CINNAMAL; POLYETHYLENE GLYCOL 1000; CYCLOHEXANE; PROPYLENE OXIDE; EDETOL; HEXYL SALICYLATE; 2-METHYL-3-(P-METHOXYPHENYL)PROPANAL; ACRYLIC ACID; ALLYL CYCLOHEXANEPROPIONATE; WATER; CARBOMER INTERPOLYMER TYPE A (ALLYL SUCROSE CROSSLINKED); DIMETHICONE PEG-8 LAURATE; GLYCERIN; .ALPHA.-PINENE; METHYLDIHYDROJASMONATE; LIMONENE, (+)-; .GAMMA.-TERPINENE; ETHYL ACETATE; NEROL; BUTYLPHENYL METHYLPROPIONAL; GERANIOL; LINALOOL

Advanced Alcohol Gel Sanitizer

Active Ingredient

Ethyl Alcohol 70%

Uses

• Hand sanitizer to reduce microorganisms on the skin.

• Use this product when soap and water are not available.

Purpose

Antiseptic

Warnings

• For external use only.

• Avoid contact with eyes. If contact occurs, rinse thoroughly with water.

• FLAMMABLE. This product contains ethyl alcohol. Keep away from

sources of ignition.

• Discontinue use if irritation or redness develops.

• If irritation persists for more than 72 hours, consult a physician.

• KEEP OUT OF REACH OF CHILDREN.

• If swallowed, get medical help or contact a Poison Control Center right away.

Directions

• Read the entire label before using this product.

• Place enough product on your palm to thoroughly cover your hands.

• Rub hands together briskly until dry.

Inactive Ingredients

Water, PEG/PPG-8/3 Laurate, Gycerin, Carbomer, Tetrahydroxypropylethylendiamine, Fragrance.

Warnings

KEEP OUT OF REACH OF CHILDREN.